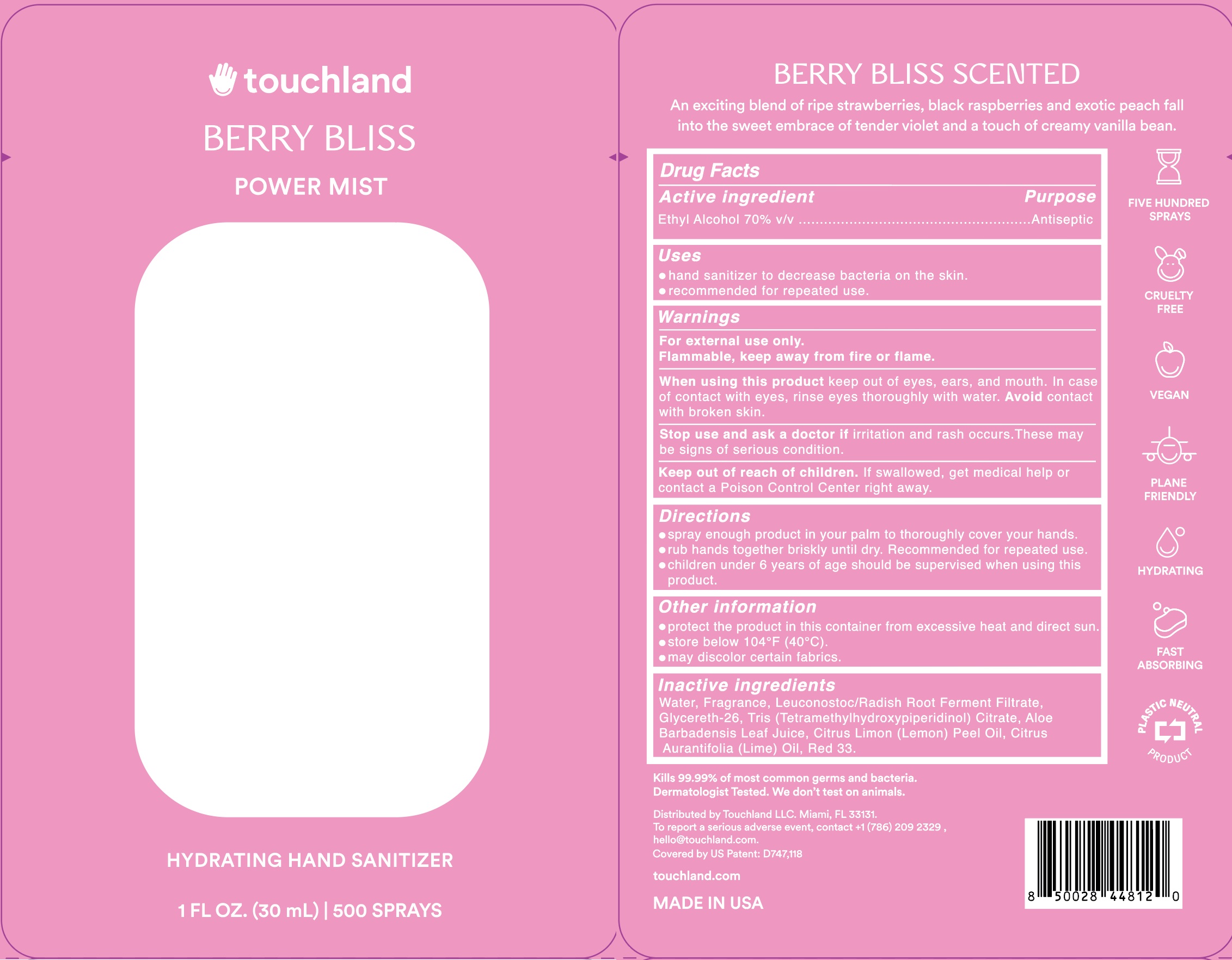 DRUG LABEL: Touchland Power Mist Hand Sanitizer Berry Bliss
NDC: 72033-102 | Form: SPRAY
Manufacturer: Touchland LLC
Category: otc | Type: HUMAN OTC DRUG LABEL
Date: 20231214

ACTIVE INGREDIENTS: ALCOHOL 0.7 mL/1 mL
INACTIVE INGREDIENTS: D&C RED NO. 33; GLYCERETH-26; LEMON OIL; ALOE VERA LEAF; LEUCONOSTOC/RADISH ROOT FERMENT FILTRATE; WATER; LIME OIL; TRIS(TETRAMETHYLHYDROXYPIPERIDINOL) CITRATE

Touchland Hand Sanitizer - Berry Bliss

Active ingredient

Ethyl Alcohol 70% v/v

Purpose

Antiseptic

Uses

hand sanitizer to decrease bacteria on the skin
recommended for repeated use

Directions

- spray enough product in your palm to thoroughly cover your hands.
- rub hands togehter briskly until dry. Recommended for repeated use.
- children under 6 years of age should be supervised when using this product

Other Information

- protect the product in this container from excessive heat and direct sun
- store below 104F (40C)
- may discolor certain fabrics

Inactive ingredients

Water, Fragrance, Leuconostoc/Radish Root Ferment Lysate Filtrate, Glycereth-26, Tris(Tetramethylhydroxypiperidinol) citrate, Aloe Barbadensis Leaf Juice, Citrus Limon (Lemon) Peel Oil, Citrus Aurantifolia (Lime) Oil, Red 33

Warnings

For external use only

Flammable, keep away from fire and flame

When using this product

keep out of eyes, ears, and mouth. In case of contact with eyes, rinse eyes thoroughly with water. Avoid contact with broken skin.

Stop use and ask a doctor if

- irritation or rash occurs. These may be signs of serious condition.

Keep out of reach of children

If swallowed, get medical help or contact an Poison Control Center right away.